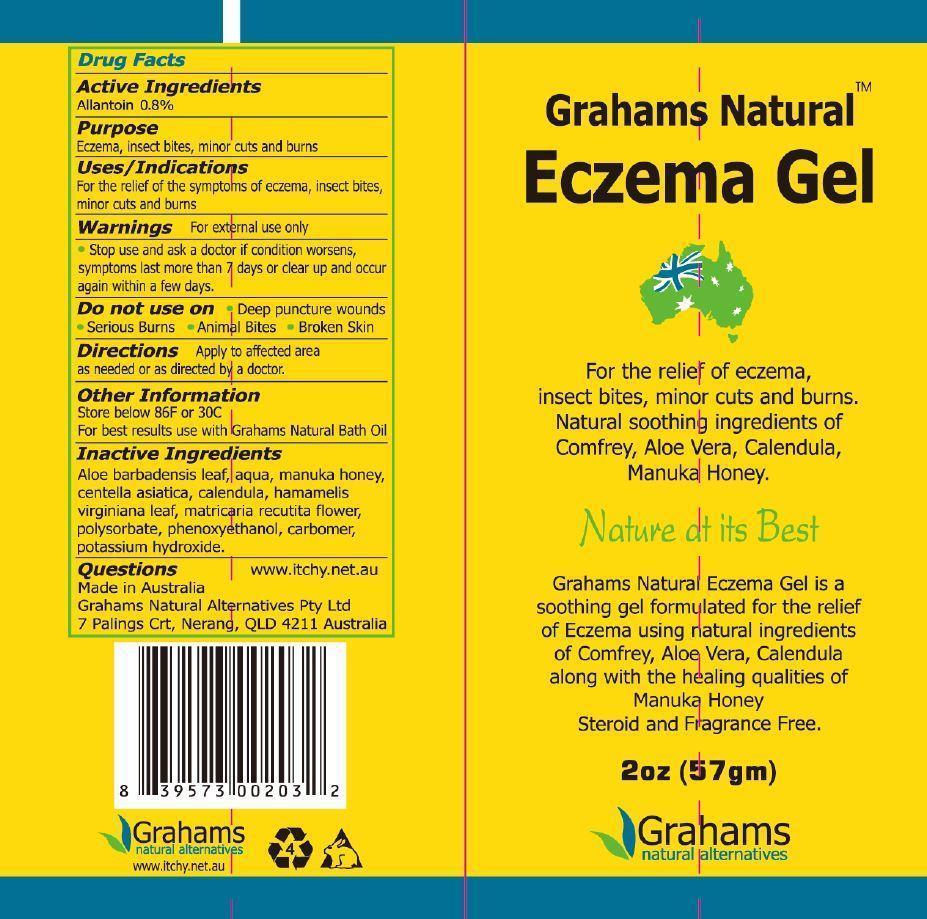 DRUG LABEL: Grahams Natural Eczema Gel
NDC: 42387-300 | Form: GEL
Manufacturer: Grahams Natural Alternatives Pty Ltd
Category: otc | Type: HUMAN OTC DRUG LABEL
Date: 20150826

ACTIVE INGREDIENTS: ALLANTOIN 0.8 g/100 g
INACTIVE INGREDIENTS: ALOE VERA LEAF; WATER; HONEY; CENTELLA ASIATICA; CALENDULA OFFICINALIS FLOWER; HAMAMELIS VIRGINIANA LEAF; MATRICARIA RECUTITA FLOWERING TOP; POLYSORBATE 20; PHENOXYETHANOL; CARBOMER COPOLYMER TYPE A; POTASSIUM HYDROXIDE

Active Ingredients

Allantoin 0.8%

Purpose

Eczema, insect bites, minor cuts and burns

Keep out of reach of children

Uses/Indications

For the relief of the symptoms of eczema, insect bites, minor cuts and burns

Directions

Apply to affected area as needed or as directed by a doctor

Warnings for external use only

Stop use and ask a doctor if condition worsens, symptoms last more than 7 days or clear up and occur again within a few days.

Do not use on

- deep puncture wounds
- serious burns
- animal bites
- broken skin

DESCRIPTION

Grahams Natural Eczema Gel

For the relief of eczema, insect bites, minor cuts and burns.

Natural soothing ingredients of comfrey, aloe vera, calendula, manuka honey.

Nature at its Best

Grahams Natural Eczema Gel is a soothing gel formulated for the relief of Eczema using natural ingredients of comfrey, aloe vera, calendula, along with the healing qualities of manuka honey

steroid and fragrance free

Other Information

Store below 86F or 30C

For best results use with Grahams Natural Bath Oil

Questions www.itchy.net.au

Made in Australia

Grahams Natural Alternatives Pty Ltd

7 Palings Crt, Nerang, QLD 4211 Australia

Inactive Ingredients

aloe barbadensis leaf, aqua, manuka honey, centella asiatica, calendula, hamamelis virginiana leaf, matricaria recutita flower, polysorbate, phenoxyethanol, carbomer, potassium hydroxide.